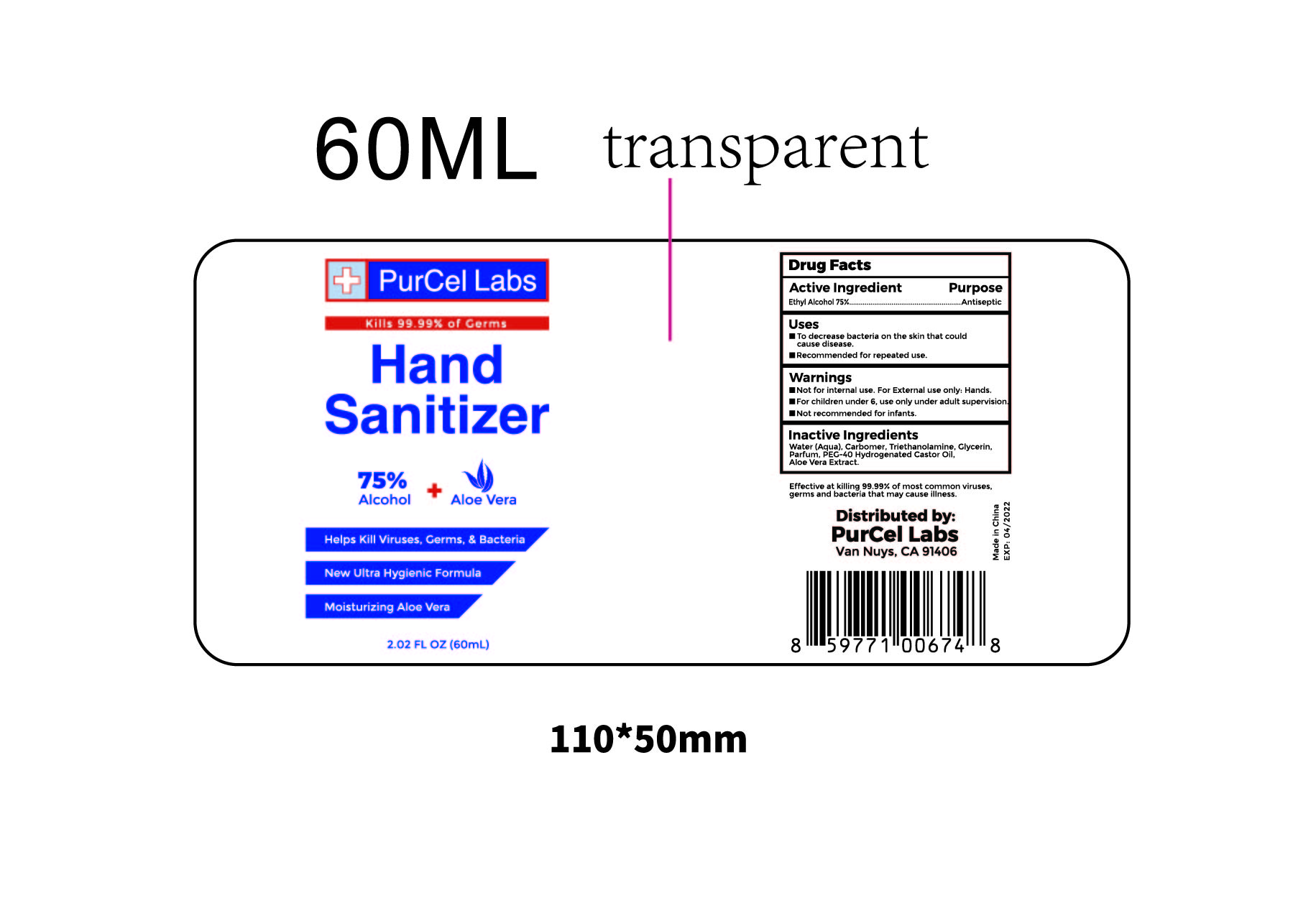 DRUG LABEL: PurCel Labs Hand Sanitizer
NDC: 76741-009 | Form: SOLUTION
Manufacturer: SUTRA BEAUTY INC
Category: otc | Type: HUMAN OTC DRUG LABEL
Date: 20200506

ACTIVE INGREDIENTS: ALCOHOL 75 mL/100 mL
INACTIVE INGREDIENTS: CARBOMER 934; TROLAMINE; GLYCERIN; ALOE VERA WHOLE

ACTIVE INGREDIENT

Ethyl Alcohol 75%

Purpose

Antiseptic

Use

To decrease bacteria on the skin that could cause disease

Recommended for repeated use

Warnings

Not for internal use. For external use only. Hands

Keep out of reach of children. If swallowed, get medical help or contact a poison control center right away

For children under 6, use only under adult supervision

Not recommended for infants

Directions

- Put enough products on your palm to cover hands and rub hands together briskly until dry

Inactive ingredients

Water, Carbomer, Triethanolamine, Glycerin, Perfume, PEG-40 Hydrogenated Castor Oil, Aloe Vera Extract